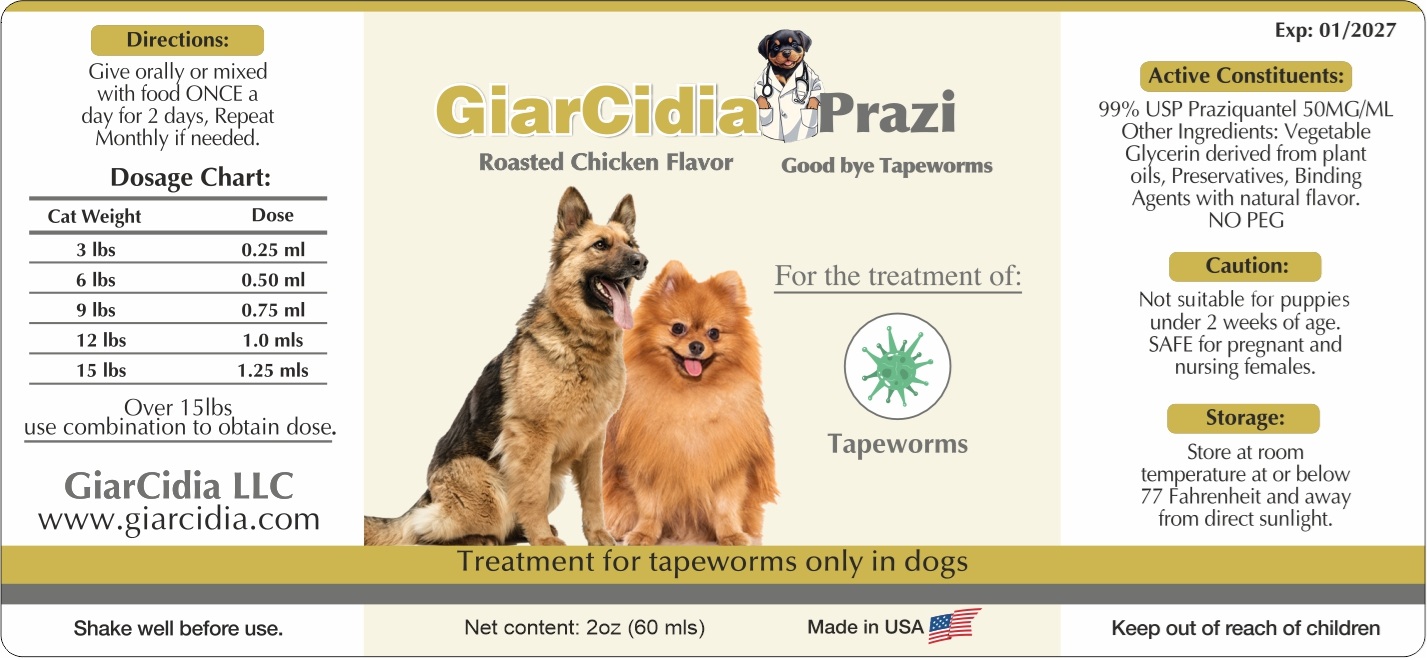 DRUG LABEL: GiarCidia Prazi
NDC: 86218-993 | Form: LIQUID
Manufacturer: GiarCidia LLC
Category: animal | Type: OTC ANIMAL DRUG LABEL
Date: 20250331

ACTIVE INGREDIENTS: PRAZIQUANTEL 50 mg/1 mL
INACTIVE INGREDIENTS: GLYCERIN; POTASSIUM SORBATE; SODIUM BENZOATE; CELLULOSE SODIUM PHOSPHATE

GiarCidia Prazi

Active Constituents:

99% USP Praziquantel 50MG/ML

Other Ingredients:

Vegetable Glycerin derived from plant oils, Preservatives, Binding Agents with natural flavor.
NO PEG

Caution:

Not suitable for puppies under 2 weeks of age. SAFE for pregnant and nursing females.

Keep out of reach of children

Storage:

Store at room temperature at or below 77 Fahrenheit and away from direct sunlight.

Directions:

Give orally or mixed with food ONCE a day for 2 days, Repeat Monthly if needed.

Dosage Chart:
Cat Weight | Dose
3 lbs | 0.25 ml
6 lbs | 0.50 ml
9 lbs | 0.75 ml
12 lbs | 1.0 mls
15 lbs | 1.25 mls
Over 15lbs use combination to obtain dose.

Roasted Chicken Flavor

Good bye Tapeworms

For the treatment of:
Tapeworms

Treatment for tapeworms only in dogs

Made in USA

GiarCidia LLC
www.giarcidia.com

Shake well before use.